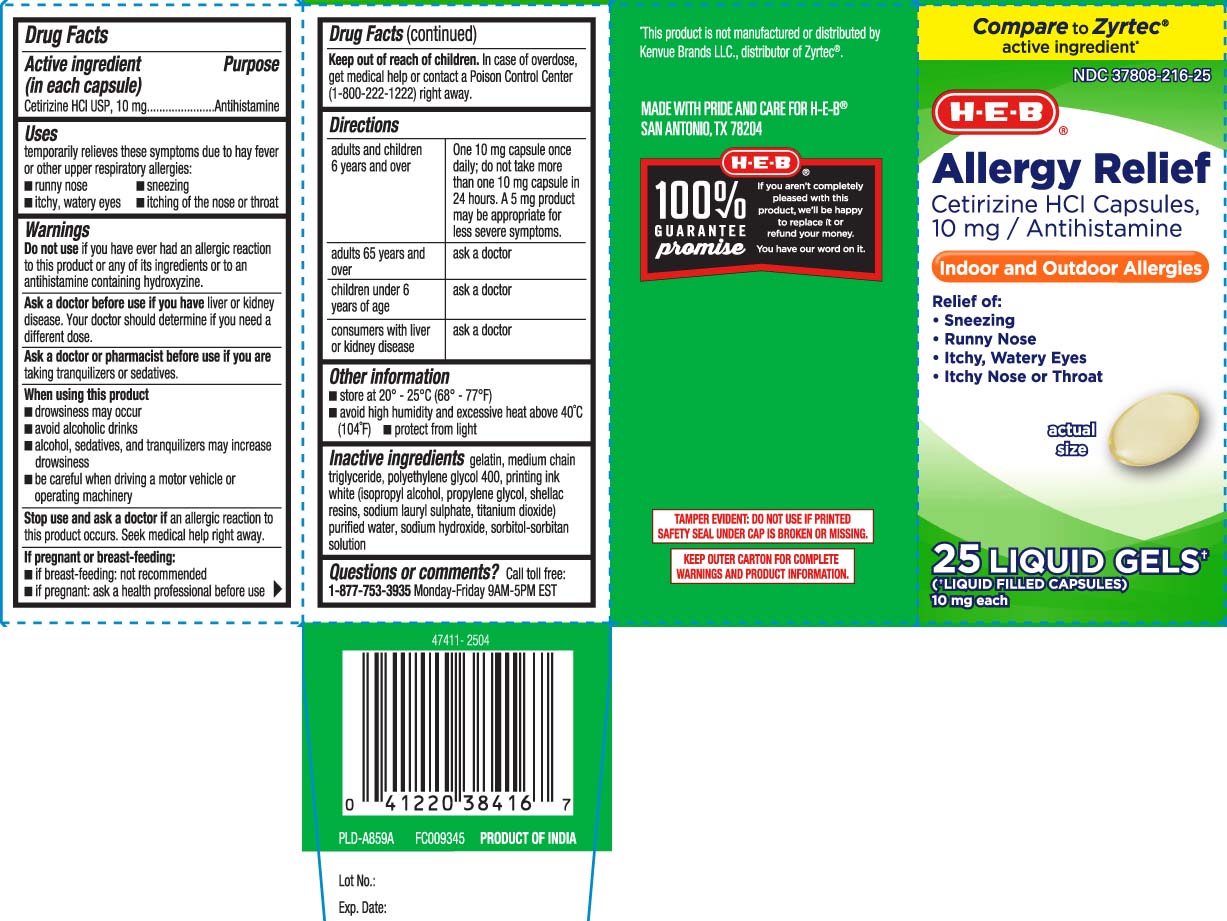 DRUG LABEL: All Day Allergy
NDC: 37808-216 | Form: CAPSULE, LIQUID FILLED
Manufacturer: H E B
Category: otc | Type: HUMAN OTC DRUG LABEL
Date: 20250502

ACTIVE INGREDIENTS: CETIRIZINE HYDROCHLORIDE 10 mg/1 1
INACTIVE INGREDIENTS: GELATIN; ISOPROPYL ALCOHOL; POLYETHYLENE GLYCOL 400; PROPYLENE GLYCOL; SODIUM HYDROXIDE; SORBITAN; SORBITOL; SHELLAC; SODIUM LAURYLSULFONATE; TITANIUM DIOXIDE; WATER; MEDIUM-CHAIN TRIGLYCERIDES

Cetirizine Hydrochloride Tablets

Active Ingredient (in each capsule)

Cetirizine HCl USP,10 mg

Purpose

Antihistamine

Uses

temporarily relieves these symptoms due to hay fever or other upper respiratory allergies:

- runny nose
- sneezing
- itchy, watery eyes
- itching of the nose or throat

Do not use

if you have ever had an allergic reaction to this product or any of its ingredients or to an antihistamine containing hydroxyzine.

Ask a doctor before use if you have

liver or kidney disease. Your doctor should determine if you need a different dose.

Ask a doctor or pharmacist before use if you are

taking tranquilizers or sedatives.

When using this product

- drowsiness may occur
- avoid alcoholic drinks
- alcohol, sedatives, and tranquilizers may increase drowsiness
- be careful when driving a motor vehicle or operating machinery

Stop use and ask a doctor if

an allergic reaction to this product occurs. Seek medical help right away.

If pregnant or breast-feeding

- if breast-feeding: not recommended
- if pregnant: ask a health professional before use.

Keep out of reach of children

In case of overdose, get medical help or contact a Poison Control Center (1-800-222-1222) right away.

Directions

Adults and children 6 years and over | One 10 mg capsule once daily; do not take more than one 10 mg capsule in 24 hours. A 5 mg product may be appropriate for less severe symptoms.
Adults 65 years and over | ask a doctor.
Children under 6 years of age | ask a doctor
Consumers with liver or kidney disease | ask a doctor

Other Information

- store at 20º -25ºC (68º - 77ºF)
- avoid high humidity and excessive heat above 40ºC (104ºF)
- protect from light

Inactive Ingredients

gelatin, medium chain triglyceride, polyethylene glycol 400, printing white ink, (isopropyl alcohol, propylene glycol, shellac resins, sodium lauryl sulphate, titanium dioxide) purified water, sodium hydroxide, sorbitan, sorbitol solution

Questions or comments?

Call toll free: 1-877-753-3935 Monday-Friday 9AM-5PM EST

Principal display panel

Compare to Zyrtec® active ingredient*

Allergy Relief

Cetirizine HCl Capsules, 10 mg /

Antihistamine

Indoor & Outdoor Allergies

Relief of:

- Sneezing
- Runny nose
- Itchy, watery eyes
- Itchy throat or nose

LIQUID GELS†

(†LIQUID FILLED CAPSULES

10 mg each

*This product is not manufactured or distributed by Kenvue Brands LLC., distributor of Zyrtec®.

TAMPER EVIDENT: DO NOT USE IF PRINTED SAFETY SEAL UNDER CAP IS BROKEN OR MISSING.

KEEP OUTER CARTON FOR COMPLETE WARNINGS AND PRODUCT INFORMATION.

MADE WITH PRIDE AND CARE FOR H-E-B®

SAN ANTONIO, TX 78204

Product Label

H-E-B Allergy Relief